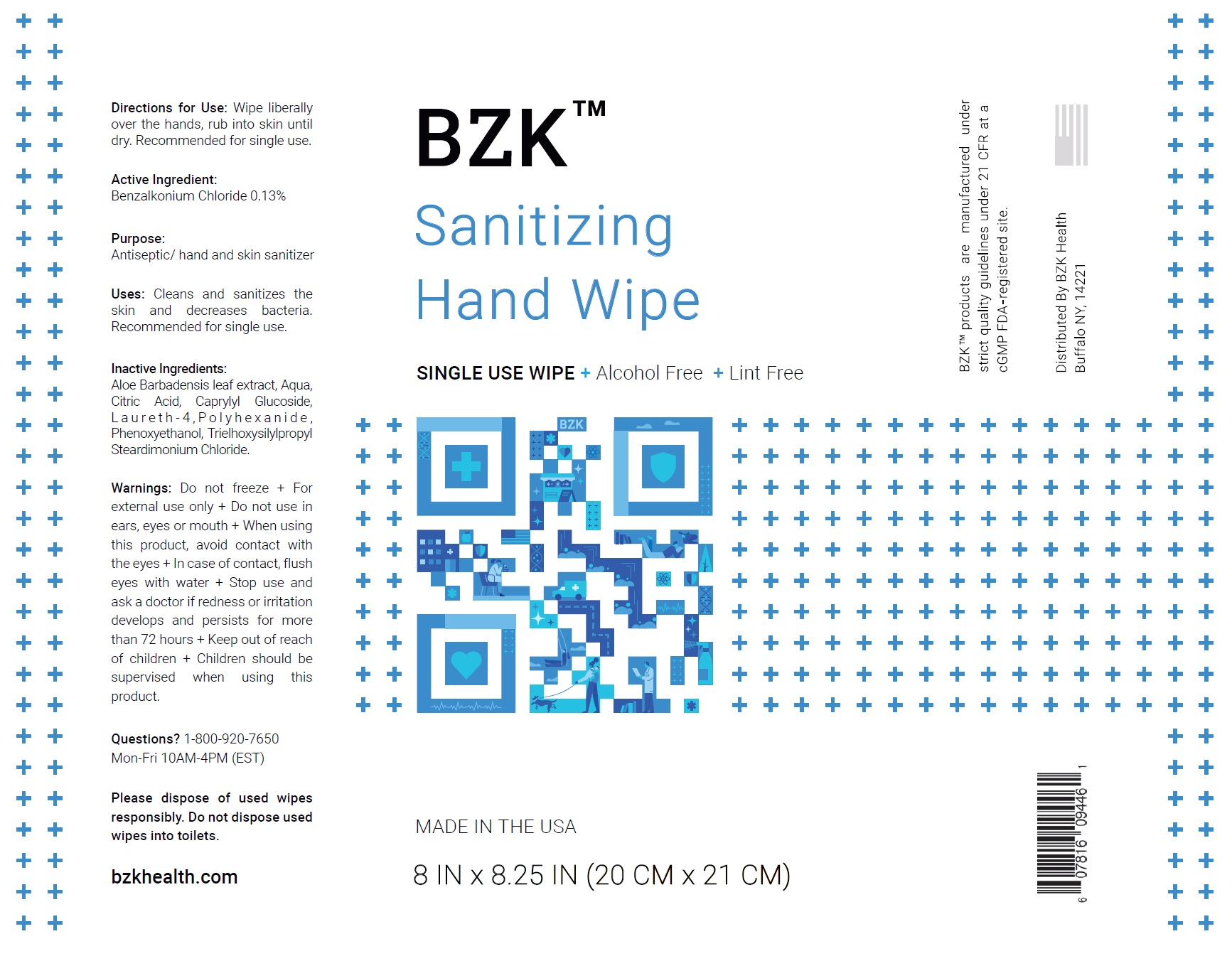 DRUG LABEL: BZK Sanitizing Hand Wipe
NDC: 81529-004 | Form: CLOTH
Manufacturer: Premium PPE, LLC
Category: otc | Type: HUMAN OTC DRUG LABEL
Date: 20210225

ACTIVE INGREDIENTS: BENZALKONIUM CHLORIDE 1.3 mg/1 mL
INACTIVE INGREDIENTS: ALOE VERA LEAF; WATER; CITRIC ACID MONOHYDRATE; CAPRYLYL GLUCOSIDE; LAURETH-4; POLIHEXANIDE; PHENOXYETHANOL; TRIETHOXYSILYLPROPYL STEARDIMONIUM CHLORIDE

BZK Sanitizing Hand Wipe

Directions for Use:

Wipe liberally over the hands, rub into skin until dry. Recommended for single use.

Active Ingredient:

Benzalkonium Chloride 0.13%

Purpose:

Antiseptic/ hand and skin sanitizer

Uses:

Cleans and sanitizes the skin and decreases bacteria. Recommended for single use.

Inactive Ingredients:

Aloe Barbadensis leaf extract, Aqua, Citric Acid, Caprylyl Glucoside, L a u r e t h - 4 , P o l y h e x a n i d e , Phenoxyethanol, Trielhoxysilylpropyl
Steardimonium Chloride.

Warnings:

Do not freeze

+ For external use only

Do not use

+ in ears, eyes or mouth

When using this product,

+avoid contact with the eyes

+ In case of contact, flush eyes with water

Stop use and ask a doctor if

+redness or irritation develops and persists for more than 72 hours

Keep out of reach of children

+Children should be supervised when using this product.

Questions?

1-800-920-7650 Mon-Fri 10AM-4PM (EST)